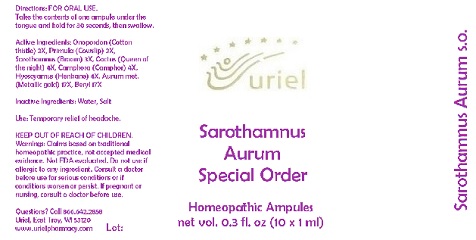 DRUG LABEL: Sarothamnus Aurum Special Order
NDC: 48951-8164 | Form: LIQUID
Manufacturer: Uriel Pharmacy Inc.
Category: homeopathic | Type: HUMAN OTC DRUG LABEL
Date: 20180524

ACTIVE INGREDIENTS: ONOPORDUM ACANTHIUM FLOWER 3 [hp_X]/1 mL; PRIMULA VERIS FLOWER 3 [hp_X]/1 mL; CYTISUS SCOPARIUS FLOWER 3 [hp_X]/1 mL; SELENICEREUS GRANDIFLORUS STEM 4 [hp_X]/1 mL; CAMPHOR (NATURAL) 4 [hp_X]/1 mL; HYOSCYAMUS NIGER LEAF 4 [hp_X]/1 mL; GOLD 17 [hp_X]/1 mL; BERYLLIUM 17 [hp_X]/1 mL
INACTIVE INGREDIENTS: WATER; SODIUM CHLORIDE

Sarothamnus Aurum Special Order

INDICATIONS AND USAGE

Directions: FOR ORAL USE.

DOSAGE AND ADMINISTRATION

Take the contents of one ampule under the tongue and hold for 30 seconds, then swallow.

ACTIVE INGREDIENT

Active Ingredients: Onopordon e flor. 3X, Primula e flor. 3X, Sarothamnus ex herba 3X, Cactus ex herba 4X, Camphora 4X, Hyoscyamus ex herba 4X, Aurum met. 17X, Beryl 17X

Inactive Ingredients: Water, Salt

PURPOSE

Use: Temporary relief of headache.

KEEP OUT OF REACH OF CHILDREN.

WARNINGS

Warnings: Claims based on traditional homeopathic practice, not accepted medical evidence. Not FDA evaluated. Do not use if allergic to any ingredient. Consult a doctor before use for serious conditions or if conditions worsen or persist. If pregnant or nursing, consult a doctor before use.

QUESTIONS

Questions? Call 866.642.2858 Uriel, East Troy, WI 53120 www.urielpharmacy.com